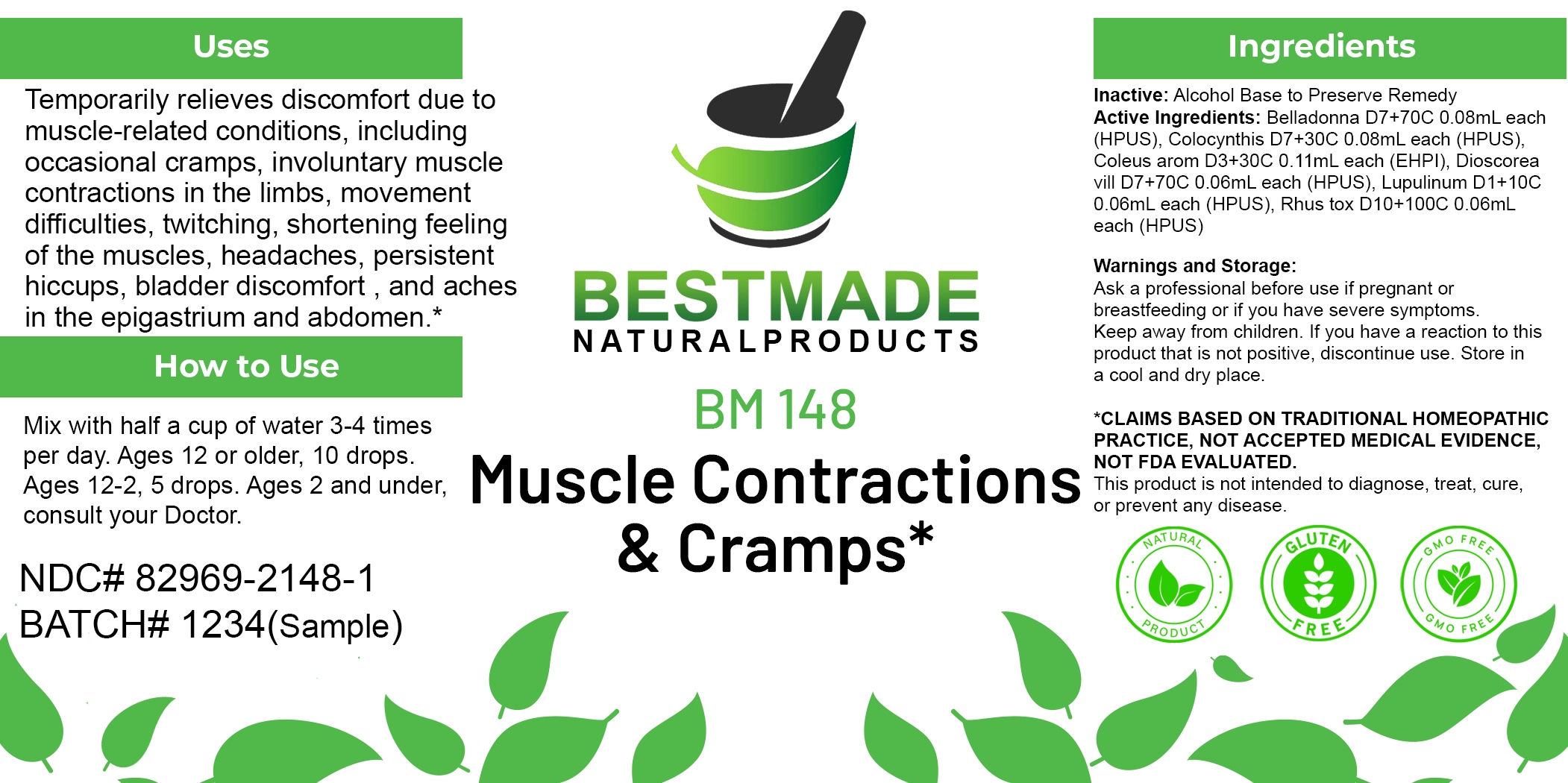 DRUG LABEL: Bestmade Natural Products BM148
NDC: 82969-2148 | Form: LIQUID
Manufacturer: Bestmade Natural Products
Category: homeopathic | Type: HUMAN OTC DRUG LABEL
Date: 20250218

ACTIVE INGREDIENTS: TOXICODENDRON PUBESCENS LEAF 30 [hp_C]/30 [hp_C]; CITRULLUS COLOCYNTHIS FRUIT PULP 30 [hp_C]/30 [hp_C]; HOPS 30 [hp_C]/30 [hp_C]; ATROPA BELLADONNA 30 [hp_C]/30 [hp_C]; COLEUS AMBOINICUS WHOLE 30 [hp_C]/30 [hp_C]; DIOSCOREA VILLOSA TUBER 30 [hp_C]/30 [hp_C]
INACTIVE INGREDIENTS: ALCOHOL 30 [hp_C]/30 [hp_C]

BM148

DOSAGE AND ADMINISTRATION

How to Use

Mix with half a cup of water 3-4 times per day. Ages 12 or older, 10 drops. Ages 12-2, 5 drops. Ages 2 and under, consult your Doctor.

Inactive:

Alcohol Base to Preserve Product

Active Ingredients:

Belladonna D7+70C 0.08mL each (HPUS), Colocynthis D7+30C 0.08mL each (HPUS), Coleus arom D3+30C 0.11mL each (EHPI), Dioscorea vill D7+70C 0.06mL each (HPUS), Lupulinum D1+10C 0.06mL each (HPUS), Rhus tox D10+100C 0.06mL each (HPUS)

Uses
Temporarily relieves discomfort due to muscle-related conditions, including occasional cramps, involuntary muscle contractions in the limbs, movement difficulties, twitching, shortening feeling of the muscles, headaches, persistent hiccups, bladder discomfort, and aches in the epigastrium and abdomen.*

Uses
Temporarily relieves discomfort due to muscle-related conditions, including occasional cramps, involuntary muscle contractions in the limbs, movement difficulties, twitching, shortening feeling of the muscles, headaches, persistent hiccups, bladder discomfort, and aches in the epigastrium and abdomen.*

KEEP OUT OF REACH OF CHILDREN

Warnings and Storage:

Ask a professional before use if pregnant or breastfeeding or if you have severe symptoms.

Keep away from children. If you have a reaction to this product that is not positive, discontinue use. Store in a cool and dry place

*CLAIMS BASED ON TRADITIONAL HOMEOPATHIC PRACTICE, NOT ACCEPTED MEDICAL EVIDENCE NOT FDA EVALUATED.
This product is not intended to diagnose, treat, cure, or prevent any disease.

Warnings and Storage:

Ask a professional before use if pregnant or breastfeeding or if you have severe symptoms.

Keep away from children. If you have a reaction to this product that is not positive, discontinue use. Store in a cool and dry place

*CLAIMS BASED ON TRADITIONAL HOMEOPATHIC PRACTICE, NOT ACCEPTED MEDICAL EVIDENCE NOT FDA EVALUATED.
This product is not intended to diagnose, treat, cure, or prevent any disease.

Entire package label